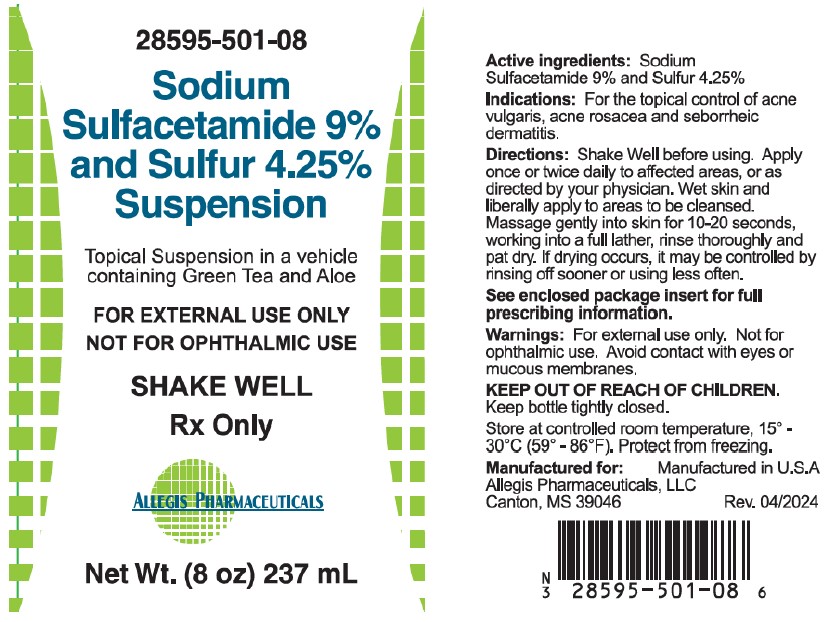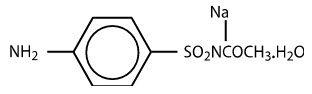 DRUG LABEL: sulfacetamide sodium and sulfur
NDC: 28595-501 | Form: SUSPENSION
Manufacturer: Allegis Pharmaceuticals, LLC
Category: prescription | Type: HUMAN PRESCRIPTION DRUG LABEL
Date: 20260211

ACTIVE INGREDIENTS: SULFACETAMIDE SODIUM 90 mg/1 mL; SULFUR 42.5 mg/1 mL
INACTIVE INGREDIENTS: CITRIC ACID ACETATE; EDETATE DISODIUM; BUTYLATED HYDROXYTOLUENE; CETYL ALCOHOL; COCAMIDOPROPYL BETAINE; GLYCERIN; GLYCERYL STEARATE SE; GREEN TEA LEAF; XANTHAN GUM; PEG-100 STEARATE; WATER; SODIUM THIOSULFATE; STEARYL ALCOHOL; TRIACETIN; ALOE VERA LEAF; SODIUM LAURETH SULFATE; PHENOXYETHANOL

Sodium Sulfacetamide 9% - Sulfur 4.25% Suspension

NDC 28595-501-08
Rx Only

Topical Suspension in a vehicle containing Green Tea and Aloe

FOR EXTERNAL USE ONLY
NOT FOR OPHTHALMIC USE

SHAKE WELL

Net Wt. (8oz) 237 mL

Active ingredients:Sodium Sulfacetamide 9% and Sulfur 4.25%

Indications:For the topical control of acne vulgaris, acne rosacea and seborrheic dermatitis.

Directions:Shake Well before using. Apply once or twice daily to affected areas, or as directed by your physician. Wet skin and liberally apply to areas to be cleansed. Massage gently into skin for 10-20 seconds, working into a full lather, rinse thoroughly and pat dry. If drying occurs, it may be controlled by rinsing off sooner or using less often.

See enclosed package insert for full prescribing information.

Warnings:For external use only. Not for ophthalmic use.

Avoid contact with eyes or mucous membranes.

KEEP OUT OF REACH OF CHILDREN.Keep bottle tightly closed.

Store at controlled room temperature, 15° - 30°C (59° - 86°F). Protect from freezing.

Manufactured for: Manufactured in U.S.A
Allegis Pharmaceuticals, LLC, Canton, MS 39046 Rev. 04-2024

Rx Only

DESCRIPTION

Sodium sulfacetamide is a sulfonamide with antibacterial activity while sulfur acts as a keratolytic agent. Chemically sodium sulfacetamide is N-[(4-aminophenyl) sulfonyl]-acetamide, monosodium salt, monohydrate. The structural formula is:

Each mL contains 90 mg of sodium sulfacetamide and 42.5 mg of sulfur in vehicle consisting of aloe vera leaf extract, butylated hydroxytoluene, cetyl alcohol, citric acid, cocamidopropyl betaine, disodium EDTA, glycerin, glyceryl stearate SE, green tea extract, PEG 100 stearate, phenoxyethanol, purified water, sodium laureth sulfate, sodium thiosulfate, stearyl alcohol, triacetin and xanthan gum.

CLINICAL PHARMACOLOGY

Sodium sulfacetamide exerts a bacteriostatic effect against sulfonamide sensitive Gram-positive and Gram-negative microorganisms commonly isolated from secondary cutaneous pyogenic infections. It acts by restricting the synthesis of folic acid required by bacteria for growth, by its competition with para-aminobenzoic acid. There is no clinical data available on the degree and rate of systemic absorption of this product when applied to the skin or scalp. However, significant absorption of sodium sulfacetamide through the skin has been reported.

The following in vitro data is available but the clinical significance is unknown. Organisms that show susceptibility to sodium sulfacetamide are: Streptococci, Staphylococci, E. coli, Klebsiella pneumoniae, Pseudomonas pyocyanea, Salmonella species, Proteus vulgaris, Nocardia and Actinomyces.

The exact mode of action of sulfur in the treatment of acne is unknown, but it has been reported that it inhibits the growth of Propionibacterium acnes and the formation of free fatty acids.

INDICATIONS

Sodium Sulfacetamide 9% - Sulfur 4.25% Suspension is indicated in the topical control of acne vulgaris, acne rosacea and seborrheic dermatitis.

CONTRAINDICATIONS

Sodium Sulfacetamide 9% - Sulfer 4.25% Supesnion is contraindicated for use by patients having known hypersensitivity to sulfonamides, sulfur or any other component of this preparation. Sodium Sulfacetamide 9% - Sulder 4.25% Supension is not to be used by patients with kidney disease.

WARNINGS

Although rare, sensitivity to sodium sulfacetamide may occur. Therefore, caution and careful supervision should be observed when prescribing this drug for patients who may be prone to hypersensitivity to topical sulfonamides. Systemic toxic reactions such as agranulocytosis, acute hemolytic anemia, purpura hemorrhagica, drug fever, jaundice and contact dermatitis indicate hypersensitivity to sulfonamides. Particular caution should be employed if areas of denuded or abraded skin are involved.

Sulfonamides are known to cause Stevens-Johnson syndrome in hypersensitive individuals. Stevens-Johnson syndrome also has been reported following the use of sodium sulfacetamide topically. Cases of drug-induced systemic lupus erythematosus from topical sulfacetamide also have been reported. In one of these cases, there was a fatal outcome.

FOR EXTERNAL USE ONLY. NOT FOR OPHTHALMIC USE.

Avoid contact with eyes, lips and mucous membranes.

KEEP OUT OF REACH OF CHILDREN.Keep container tightly closed.

PRECAUTIONS

General

Nonsusceptible organisms, including fungi, may proliferate with the use of this preparation. If irritation develops, use of the product should be discontinued and appropriate therapy instituted. Patients should be carefully observed for possible local irritation or sensitization during long-term therapy. Systemic absorption of topical sulfonamides is greater following application to large, infected, abraded, denuded or severely burned areas. Under these circumstances, any of the adverse effects produced by the systemic administration of these agents could potentially occur, and appropriate observations and laboratory determinations should be performed.

The object of this therapy is to achieve desquamation without irritation, but sodium sulfacetamide and sulfur can cause reddening and scaling of the epidermis. These side effects are not unusual in the treatment of acne vulgaris, but patients should be cautioned about the possibility.

Information for patients

Avoid contact with eyes, lips and mucous membranes. Patients should discontinue the use of this product if the condition becomes worse or if a rash develops in the area being treated or elsewhere. The use of this product should also be discontinued promptly and the physician notified if any arthritis, fever or sores in the mouth develop.

Drug Interactions

This product is incompatible with silver preparations.

Carcinogenesis, Mutagenesis and Impairment of Fertility

Long-term studies in animals have not been performed to evaluate carcinogenic potential. Studies on reproduction and fertility also have not been performed. Chromosomal nondisjunction has been reported in the yeast, Saccharomyces cerevisiae, following application of sodium sulfacetamide. The significance of this finding to the topical use of sodium sulfacetamide in the human is unknown.

PREGNANCY

Category C

Animal reproduction studies have not been conducted with Sodium Sulfacetamide 9% - Sulfer 4.25% Suspension. It is not known whether Sodium Sulfacetamide 9% - Sulfer 4.25% Suspension can cause fetal harm when administered to a pregnant woman or can affect reproduction capacity. Sodium Silfacetamide 9% - Sulfer 4.25% should be given to a pregnant woman only if clearly needed or when potential benefits outweigh potential hazards to the fetus.

NURSING MOTHERS

It is not known whether this drug is excreted in the human milk. However, small amounts of orally administered sulfonamides have been reported to be eliminated in human milk. In view of this and because many drugs are excreted in human milk, caution should be exercised when Sodium Sulfacetamide 9% - Sulfur 4.25% Supesnion is administered to a nursing woman.

PEDIATRIC USE

Safety and effectiveness in children under the age of 12 have not been established.

ADVERSE REACTIONS

Reports of irritation and hypersensitivity to sodium sulfacetamide are uncommon. The following adverse reactions, reported after administration of sterile ophthalmic sodium sulfacetamide, are noteworthy: instances of Stevens-Johnson syndrome and instances of local hypersensitivity which progressed to a syndrome resembling systemic lupus erythematosus; in one case a fatal outcome was reported (see WARNINGS).

Call your doctor for medical advice about side effects. To report SUSPECTED ADVERSE REACTIONSor obtain product information, contact Allegis Pharmacuticals, LLC at 1-866-633-9033 or FDA at 1-800-FDA-1088 or www.fda.gov/medwatch.

OVERDOSAGE

The oral LD50 of sulfacetamide in mice is 16.5 g/kg. In the event of overdosage, emergency treatment should be started immediately.

Manifestations

Overdosage may cause nausea and vomiting. Large oral overdosage may cause hematuria, crystalluria and renal shutdown due to the precipitation of sulfa crystals in the renal tubules and the urinary tract. For treatment, contact your local Poison Control Center (1-800-222-1222), or your doctor.

DOSAGE AND ADMINISTRATION

SHAKE WELL before use.Cleanse affected areas. Apply Sodium Sulfacetamide 9% - Sulfer 4.25% Suspension once or twice daily to affected areas, or as directed by your physician. Wet skin and liberally apply to areas to be cleansed. Massage gently into skin for 10-20 seconds, working into a full lather, rinse thoroughly and pat dry. If skin dryness occurs, it may be controlled by rinsing off Sodium Sulfacetamide 9% - Sulfer 4.25% sooner or using less often.

HOW SUPPLIED

Sodium Sulfacetamide 9% - Sulfur 4.25% Suspension is available in 8 fl oz (237 mL) bottles, NDC 28595-501-08.

STORAGE AND HANDLING

Store at controlled room temperature, 15° - 30°C (59° - 86°F). Protect from freezing.

KEEP THIS AND ALL MEDICATIONS OUT OF THE REACH OF CHILDREN.

Manufactured for:
Allegis Pharmaceuticals, LLC
Canton, MS 39046

Manufactured in U.S.A

Rev. 04/2024

All prescriptions using this product shall be made subject to state and federal statutes as applicable. NOTE: this is not an Orange Book product and has not been subjected to FDA therapeutic equivalency or other equivalency testing.

PRINCIPAL DISPLAY PANEL - 237 mL Bottle Label

NDC 28595-501-08

Rx Only

Sodium Sulfacetamide 9% Sulfur 4.25% Suspension

Topical Suspension in a vehicle containing
Green Tea and Aloe

FOR EXTERNAL USE ONLY
NOT FOR OPHTHALMIC USE

SHAKE WELL

Net Wt. (8oz) 237mL

Allegis Pharmaceuticals, LLC

Canton MS 39046